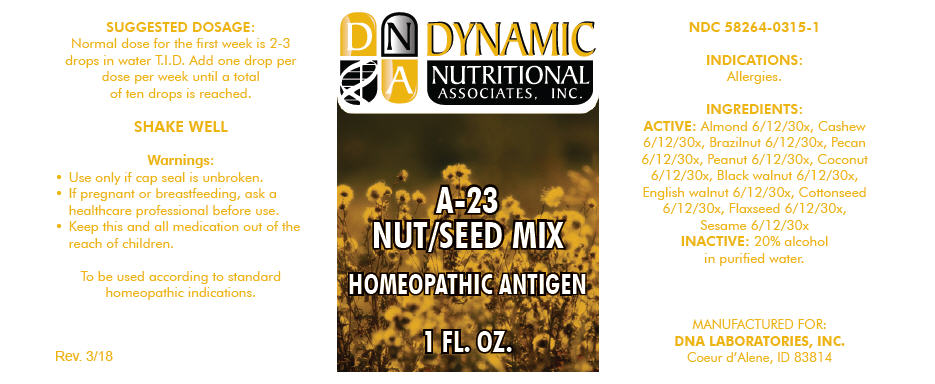 DRUG LABEL: A-23
NDC: 58264-0315 | Form: SOLUTION
Manufacturer: DNA Labs, Inc.
Category: homeopathic | Type: HUMAN OTC DRUG LABEL
Date: 20250109

ACTIVE INGREDIENTS: ALMOND 30 [hp_X]/1 mL; CASHEW 30 [hp_X]/1 mL; BRAZIL NUT 30 [hp_X]/1 mL; PECAN 30 [hp_X]/1 mL; PEANUT 30 [hp_X]/1 mL; COCONUT 30 [hp_X]/1 mL; BLACK WALNUT 30 [hp_X]/1 mL; ENGLISH WALNUT 30 [hp_X]/1 mL; COTTON SEED 30 [hp_X]/1 mL; FLAX SEED 30 [hp_X]/1 mL; SESAME SEED 30 [hp_X]/1 mL
INACTIVE INGREDIENTS: ALCOHOL; WATER

A-23

NDC 58264-0315-1

INDICATIONS

PURPOSE

Allergies.

INGREDIENTS

ACTIVE

Almond 6/12/30x, Cashew 6/12/30x, Brazilnut 6/12/30x, Pecan 6/12/30x, Peanut 6/12/30x, Coconut 6/12/30x, Black walnut 6/12/30x, English walnut 6/12/30x, Cottonseed 6/12/30x, Flaxseed 6/12/30x, Sesame 6/12/30x

INACTIVE

20% alcohol in purified water.

SUGGESTED DOSAGE

Normal dose for the first week is 2-3 drops in water T.I.D. Add one drop per dose per week until a total of ten drops is reached.

STORAGE AND HANDLING

SHAKE WELL

Warnings

- Use only if cap seal is unbroken.

PREGNANCY OR BREAST FEEDING

- If pregnant or breastfeeding, ask a healthcare professional before use.

KEEP OUT OF REACH OF CHILDREN

- Keep this and all medication out of the reach of children.

To be used according to standard homeopathic indications.

PRINCIPAL DISPLAY PANEL - 1 FL. OZ. Bottle Label

DYNAMIC
NUTRITIONAL
ASSOCIATES, INC.

A-23
NUT/SEED MIX

HOMEOPATHIC ANTIGEN

1 FL. OZ.